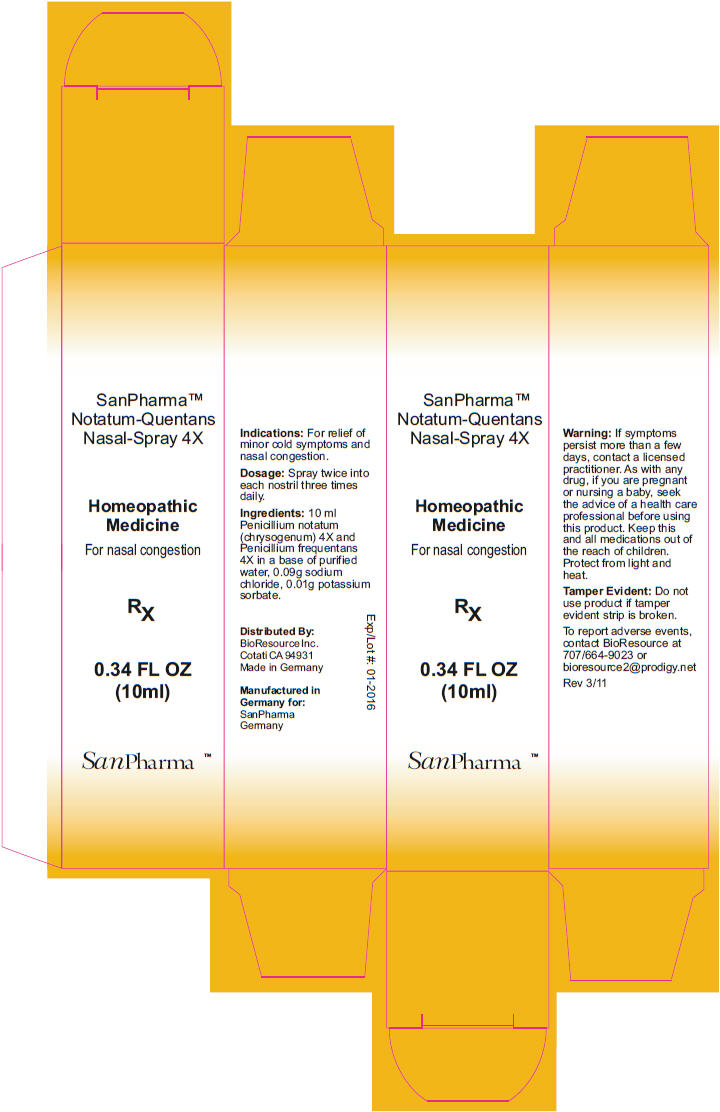 DRUG LABEL: Notatum-Quentans Nasal 4X
NDC: 54256-046 | Form: SPRAY
Manufacturer: BioResource Inc.
Category: homeopathic | Type: HUMAN OTC DRUG LABEL
Date: 20160126

ACTIVE INGREDIENTS: Penicillium Chrysogenum Var. Chrysogenum 4 [hp_X]/10 mL; Penicillium Glabrum 4 [hp_X]/10 mL
INACTIVE INGREDIENTS: Water; Sodium chloride; Potassium sorbate

Notatum-Quentans Nasal Spray 4X

PURPOSE

Indications

For relief of minor cold symptoms and nasal congestion.

Dosage

Spray twice into each nostril three times daily.

ACTIVE INGREDIENT

Ingredients

10 ml Penicillium notatum (chrysogenum) 4X and Penicillium frequentans 4X in a base of purified water, 0.09g sodium chloride, 0.01g potassium sorbate.

Warning

If symptoms persist more than a few days, contact a licensed practitioner.

PREGNANCY OR BREAST FEEDING

As with any drug, if you are pregnant or nursing a baby, seek the advice of a health care professional before using this product.

KEEP OUT OF REACH OF CHILDREN

Keep this and all medications out of the reach of children. Protect from light and heat.

Tamper Evident

Do not use product if tamper evident strip is broken.

To report adverse events, contact BioResource at 707/664-9023 or bioresource2@prodigy.net

Distributed By:
BioResource Inc.
Cotati CA 94931

PRINCIPAL DISPLAY PANEL - 10 ml Bottle Box

SanPharma™
Notatum-Quentans
Nasal-Spray 4X

Homeopathic
Medicine

For nasal congestion

RX

0.34 FL OZ
(10ml)

SanPharma ™